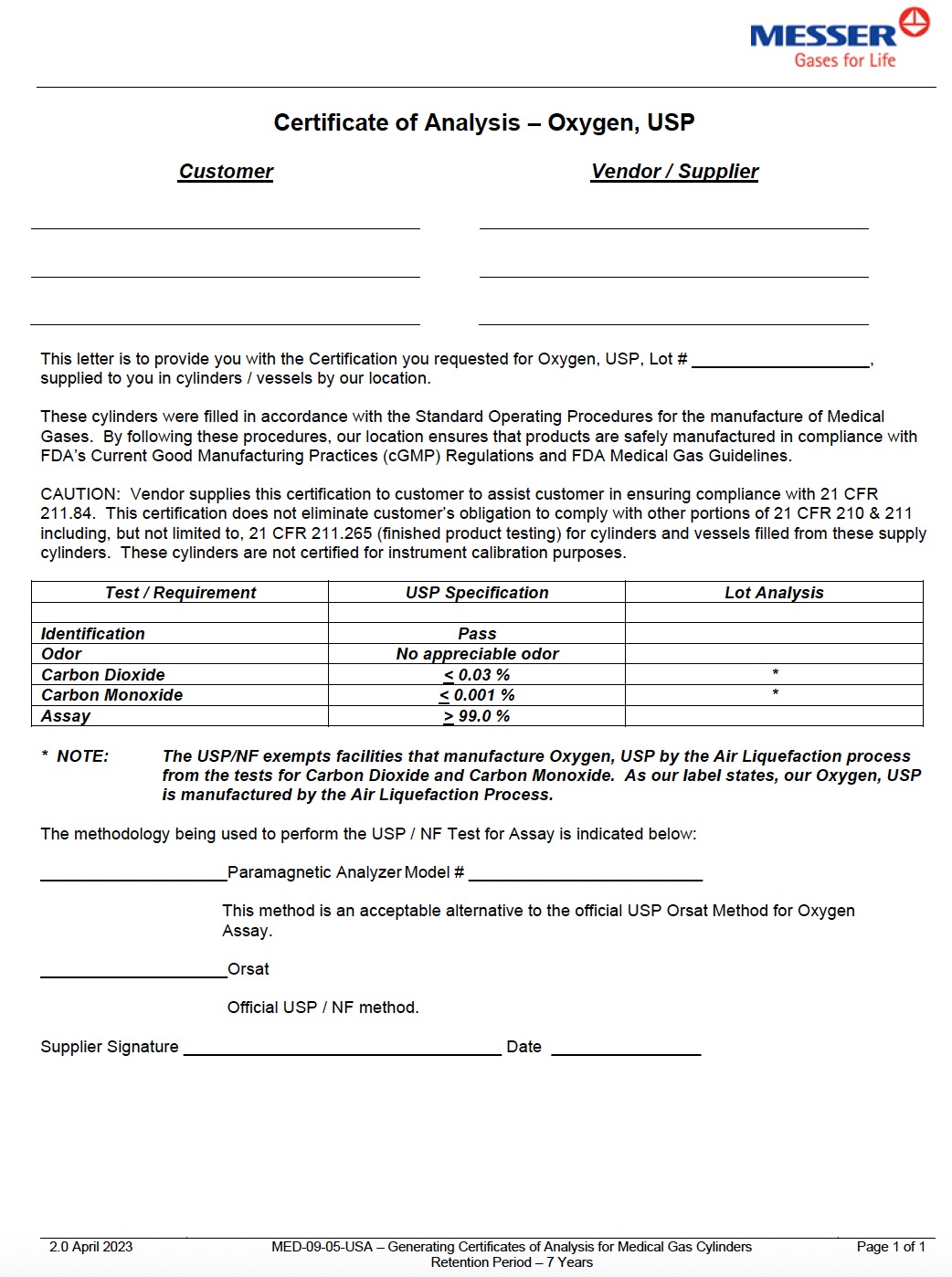 DRUG LABEL: Oxygen
NDC: 52374-011 | Form: GAS
Manufacturer: Messer Gas Puerto Rico, Inc
Category: prescription | Type: HUMAN PRESCRIPTION DRUG LABEL
Date: 20251118

ACTIVE INGREDIENTS: OXYGEN 995 mL/1 L

Messer PR - Oxygen USP Bulk Liquid -011

PACKAGE LABEL

Certificate of Analysis – Oxygen, USP

Customer Vendor / Supplier
This letter is to provide you with the Certification you requested for Oxygen, USP, Lot #,
supplied to you in cylinders / vessels by our location.

These cylinders were filled in accordance with the Standard Operating Procedures for the manufacture of Medical
Gases. By following these procedures, our location ensures that products are safely manufactured in compliance with
FDA’s Current Good Manufacturing Practices (cGMP) Regulations and FDA Medical Gas Guidelines.

CAUTION: Vendor supplies this certification to customer to assist customer in ensuring compliance with 21 CFR
211.84. This certification does not eliminate customer’s obligation to comply with other portions of 21 CFR 210 & 211
including, but not limited to, 21 CFR 211.265 (finished product testing) for cylinders and vessels filled from these supply
cylinders. These cylinders are not certified for instrument calibration purposes.

Test / Requirement

USP Specification

Lot Analysis

Identification

Pass

Odor

No appreciable odor

Carbon Dioxide

< 0.03 %

*

Carbon Monoxide

≤ 0.001 %

*

Assay

> 99.0 %

NOTE: The USP/NF exempts facilities that manufacture Oxygen, USP by the Air Liquefaction process
from the tests for Carbon Dioxide and Carbon Monoxide. As our label states, our Oxygen, USP
is manufactured by the Air Liquefaction Process.

The methodology being used to perform the USP / NF Test for Assay is indicated below:

Paramagnetic Analyzer Model #

This method is an acceptable alternative to the official USP Orsat Method for Oxygen Assay.

Orsat

Official USP / NF method.

Supplier Signature Date